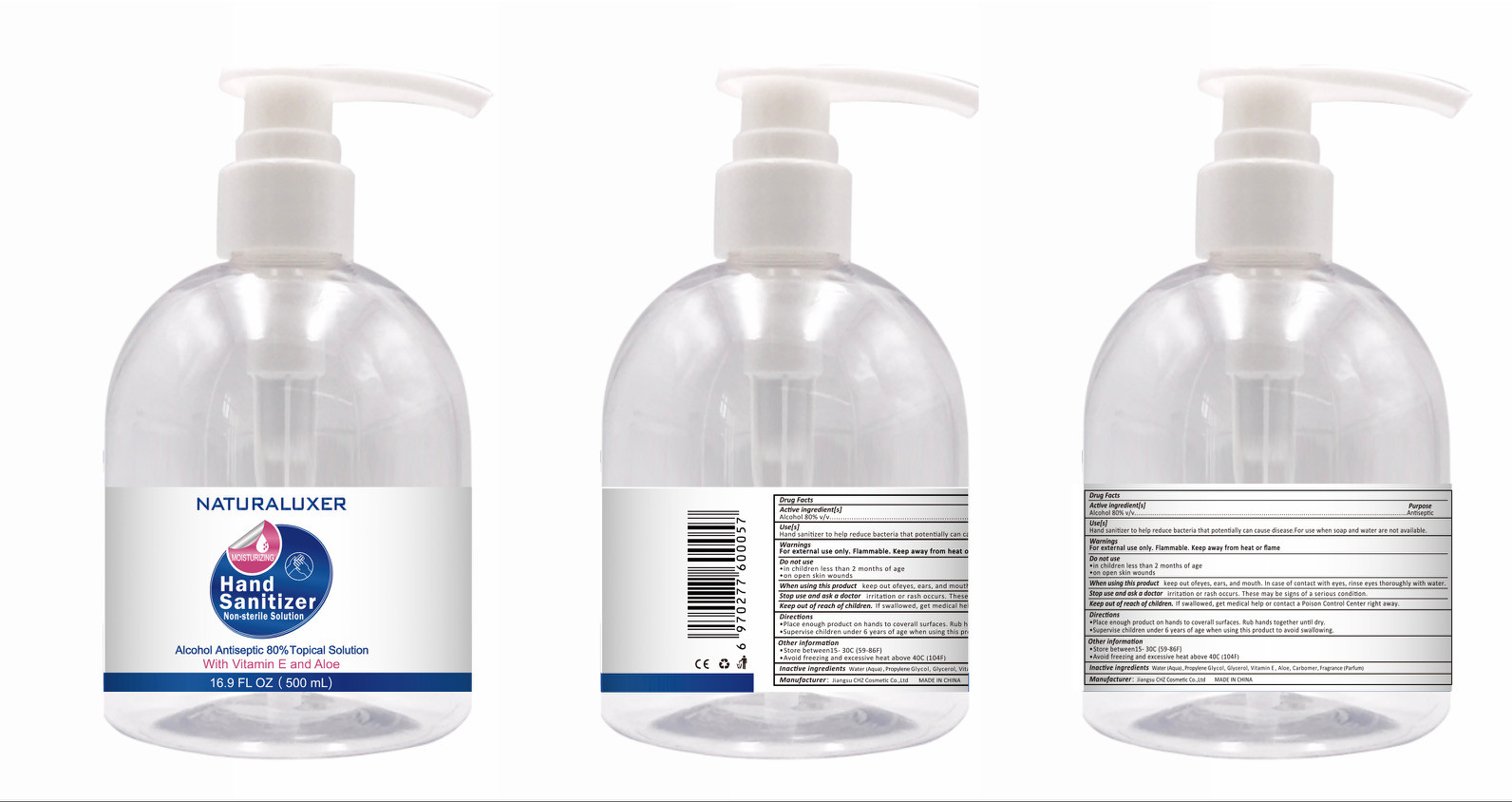 DRUG LABEL: Hand Sanitizer
NDC: 54284-004 | Form: LIQUID
Manufacturer: Jiangsu CHZ Cosmetic Co., Ltd.
Category: otc | Type: HUMAN OTC DRUG LABEL
Date: 20200509

ACTIVE INGREDIENTS: ALCOHOL 400 mL/500 mL
INACTIVE INGREDIENTS: FRAGRANCE LAVENDER & CHIA F-153480; .ALPHA.-TOCOPHEROL; GLYCERIN; ALOE; PROPYLENE GLYCOL; WATER; CARBOMER HOMOPOLYMER, UNSPECIFIED TYPE

PURPOSE

Disinfection
Sterilization

ACTIVE INGREDIENT

Alcohol

INACTIVE INGREDIENT

Water（Aqua）

Glycerol

Propylene Glycol

Aloe

Corbomer

Vitamin E

Fragrance(parfum)

keep out of reach of children

INDICATIONS AND USAGE

Place enough product on hands to cover all surfaces. Rub hands together until dry.

WARNINGS

For external use only. Flammable. Keep away from heat or flame

DOSAGE AND ADMINISTRATION

Disinfection
Sterilization
No Rinseing